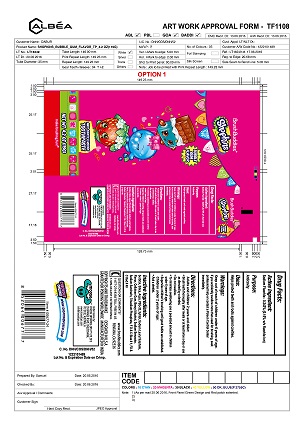 DRUG LABEL: Shopkins Brush Buddies
NDC: 70108-005 | Form: PASTE
Manufacturer: Ashtel Studios Inc.
Category: otc | Type: HUMAN OTC DRUG LABEL
Date: 20191231

ACTIVE INGREDIENTS: SODIUM FLUORIDE 2.4 mg/100 g
INACTIVE INGREDIENTS: SODIUM PHOSPHATE, TRIBASIC, DODECAHYDRATE; CARBOXYMETHYLCELLULOSE SODIUM, UNSPECIFIED FORM; SORBITOL; SILICA DIMETHYL SILYLATE; WATER; .ALPHA.-(.ALPHA.-AMINOPROPYL)BENZYL ALCOHOL; POLYETHYLENE GLYCOL 1600; XYLITOL; SODIUM LAURYL SULFATE; SODIUM BENZOATE; SACCHARIN SODIUM

Shopkins Brush Buddies

PURPOSE

Anticavity

Keep out of reach of children. In case of accidental digestion seek professional assistance or contact a poison control center immediately.

Active Ingredient Purpose

Sodium Fluoride 0.243% (0.15% w/v fluoride ion) ......................... Anticavity

INDICATIONS AND USAGE

Helps protect teeth and roots against cavities

keep out of reach of children under 6 years of age.

If you accidentally swallow more than used for brushing, seek professional help or contact a poison control center immediately

INACTIVE INGREDIENT

Sorbitol, Silica, Aqua, PEG-32, Xylitol, Sodium Lauryl Sulphate, Flavor, Cellulose Gum, Benzyl Alcohol, Sodium Benzoate, Sodium Saccharin, Trisodium Phosphate, FD & C Blue #1, FD &C Red # 40

DOSAGE AND ADMINISTRATION

Adults and children 2 years and older:
Brush teeth thoroughly after meals or at least twice a day or use as directed by a dentist.
Do not swallow
To minimize swallowing use a pea-sized amount in children under 6 years of age.
Supervise children's brushing until good habits are established.
Children under 2 years of age: Ask a dentist.